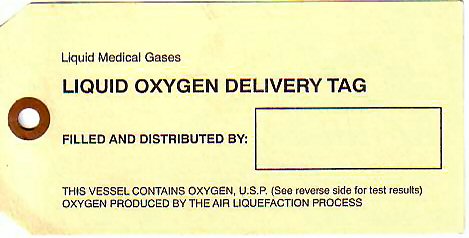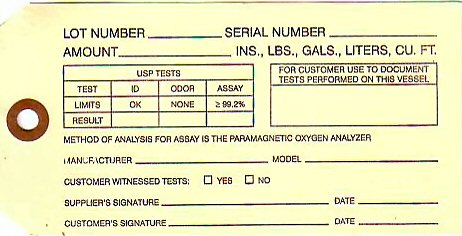 DRUG LABEL: OXYGEN
NDC: 57236-0001 | Form: GAS
Manufacturer: Saginaw Weldilng Supply Company
Category: prescription | Type: HUMAN PRESCRIPTION DRUG LABEL
Date: 20100101

ACTIVE INGREDIENTS: OXYGEN 99 L/100 L

OXYGEN CERTIFICATE OF ANALYSIS

LOT NUMBER_____________ SERIAL NUMBER__________ AMOUNT__________INS, LBS., GALS., LITERS, CU. FT.
USP TESTS
TEST ID ODOR ASSAY
LIMITS OK NONE LESS THAN 99.2%
RESULT
FOR CUSTOMER TO USE TO DOCUMENT TESTS PERFORMED ON THIS VESSEL
METHOD OF ANALYSIS FOR ASSAY IS THE PARAMAGNETIC OXYGEN ANALYZER MANUFACTURER__________ MODEL______________ CUSTOMER WITNESSED TESTS YES NO SUPPLIERS SIGNATURE__________ DATE____________ CUSTOMERS SIGNATURE_______________ DATE________________
LIQUID MEDICAL GASES LIQUID OXYGEN DELIVERY TAG FILLED AND DISTRIBUTED BY____________ THIS VESSEL CONTAINS OXYGEN USP (SEE REVERSE SIDE FOR TEST RESULTS) OXYGEN PRODUCED BY THE AIR LIQUEFACTION PROCESS